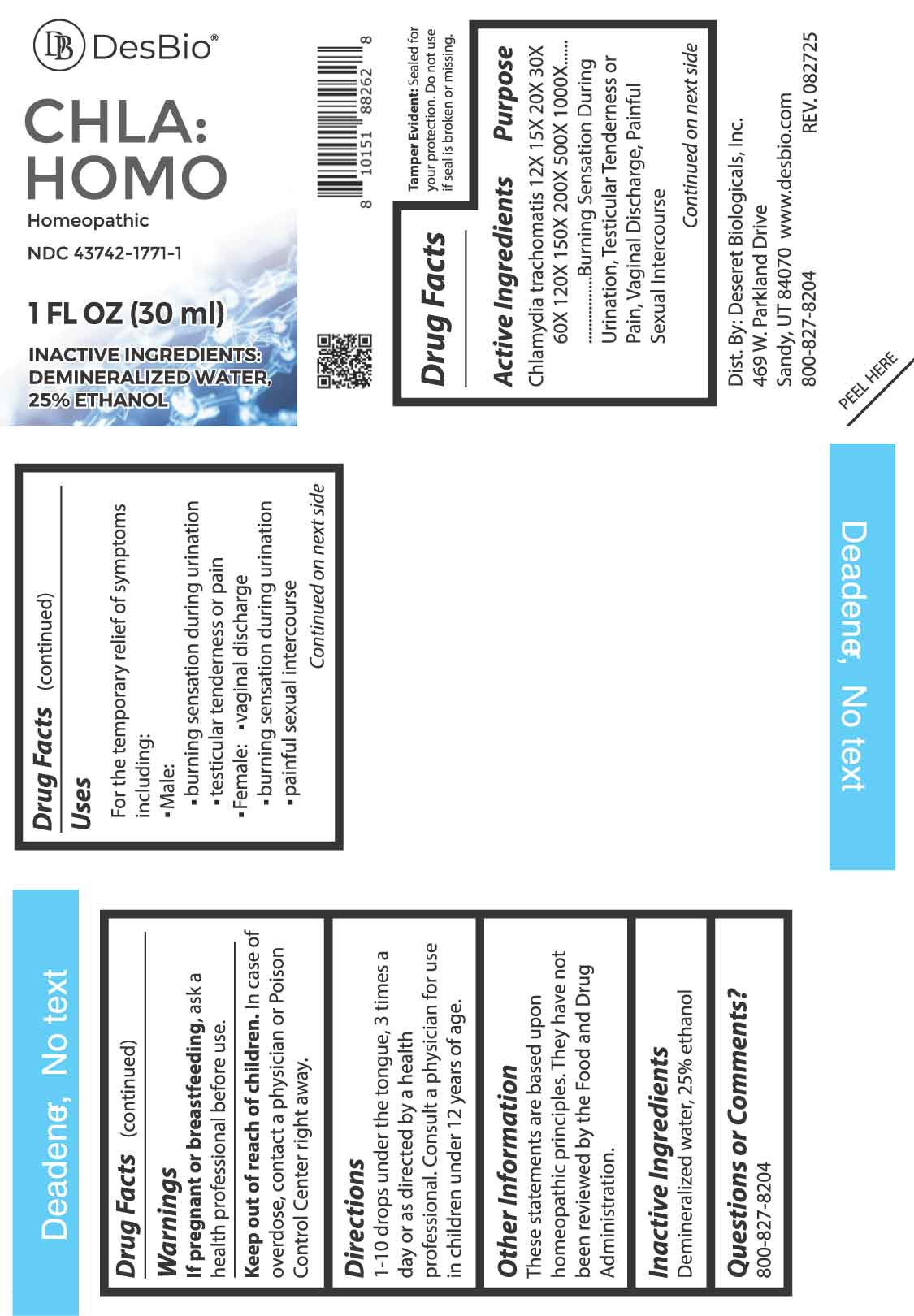 DRUG LABEL: CHLA HOMO
NDC: 43742-1771 | Form: LIQUID
Manufacturer: Deseret Biologicals, Inc.
Category: homeopathic | Type: HUMAN OTC DRUG LABEL
Date: 20251203

ACTIVE INGREDIENTS: CHLAMYDIA TRACHOMATIS 12 [hp_X]/1 mL
INACTIVE INGREDIENTS: WATER; ALCOHOL

DRUG FACTS:

ACTIVE INGREDIENTS:

Chlamydia Trachomatis 12X, 15X, 20X, 30X, 60X, 120X, 150X, 200X, 500X, 1000X.

PURPOSE:

Chlamydia trachomatis - Burning Sensation During Urination, Testicular Tenderness or Pain, Vaginal Discharge, Painful Sexual Intercourse.

These statements are based upon homeopathic principles. They have not been reviewed by the Food and Drug Administration.

USES:

For temporary relief of symptoms including:

• Male:

• burning sensation during urination

• testicular tenderness or pain

• Female:

• vaginal discharge

• burning sensation during urination

• painful sexual intercourse

These statements are based upon homeopathic principles. They have not been reviewed by the Food and Drug Administration.

WARNINGS:

If pregnant or breastfeeding, ask a health professional before use.

Keep out of reach of children. In case of overdose, contact a physician or Poison Control Center right away.

Tamper Evident: Sealed for your protection. Do not use if seal is broken or missing.

KEEP OUT OF REACH OF CHILDREN:

In case of overdose, contact a physician or Poison Control Center right away.

DIRECTIONS:

1-10 drops under the tongue, 3 times a day or as directed by a health professional. Consult a physician for use in children under 12 years of age.

INACTIVE INGREDIENTS:

Demineralized water, 25% ethanol

QUESTIONS:

Dist. By: Deseret Biologicals, Inc.

469 W. Parkland Drive

Sandy, UT 8407

www.desbio.com

800-827-8204

PACKAGE LABEL DISPLAY:

DesBio

CHLA:HOMO

Homeopathic

NDC 43742-1771-1

1 FL OZ (30 ml)